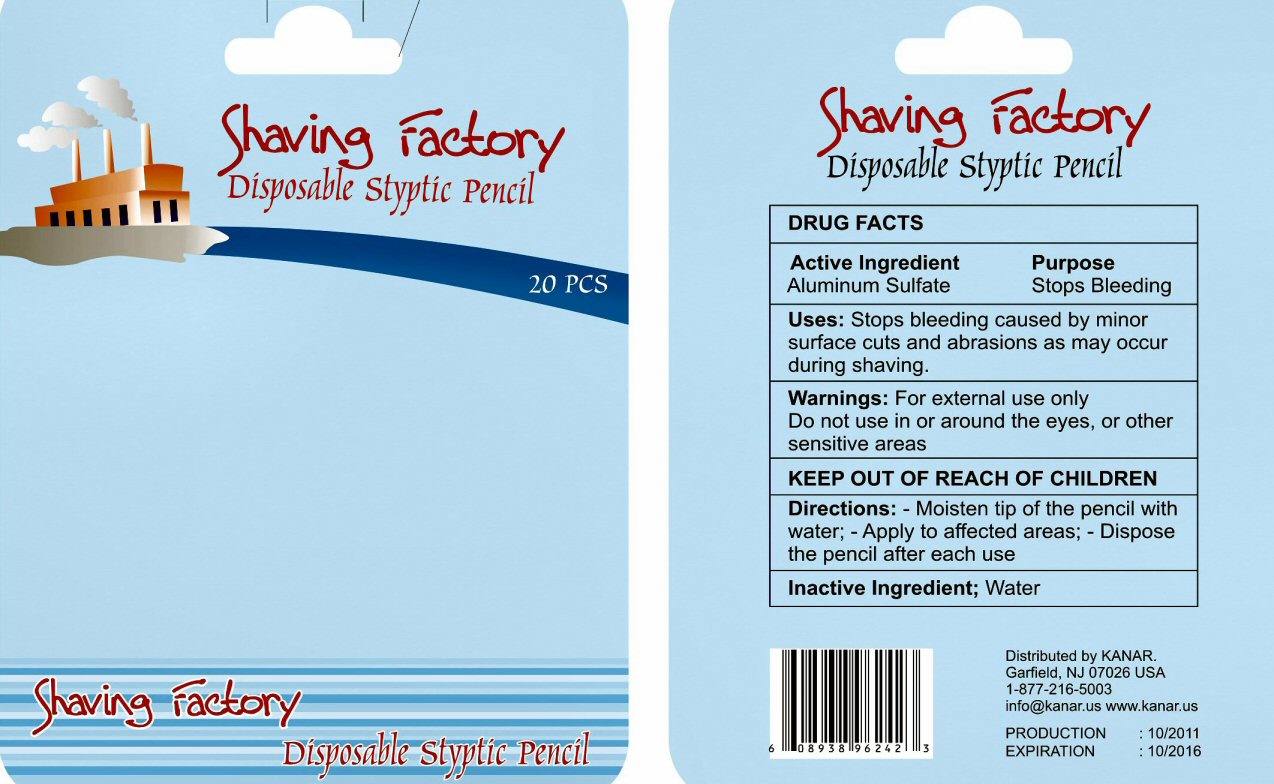 DRUG LABEL: Shaving Factory
NDC: 76499-002 | Form: STICK
Manufacturer: Derby International LLC
Category: otc | Type: HUMAN OTC DRUG LABEL
Date: 20120330

ACTIVE INGREDIENTS: ALUMINUM SULFATE 9 mL/10 mL
INACTIVE INGREDIENTS: WATER

Active Ingredients

DRUG FACTS Active Ingredient Aluminum Sulfate

Purpose

Purpose Stops Bleeding

Keep Out Of Reach Of Children

Uses

Uses: Stops bleeding caused by minor surface cuts and abrasions as may occur during shaving.

Warnings

Warnings: For external use only. Do not use in or around the eyes, or other sensitive areas.

Directions

Directions: - Moisten tip of the pencil with water; - Apply to affected areas; - Dispose the pencil after each use

Inactive Ingredient

Inactive Ingredient; Water

Package Label

Shaving Factory Disposable Styptic Pencil 20 PCS

Distributed by KANAR Garfield, NJ 07026 USA 1-877-216-5003 info@kanar.us www.kanar.us

PRODUCTION :10/2011 EXPIRATION :10/2016